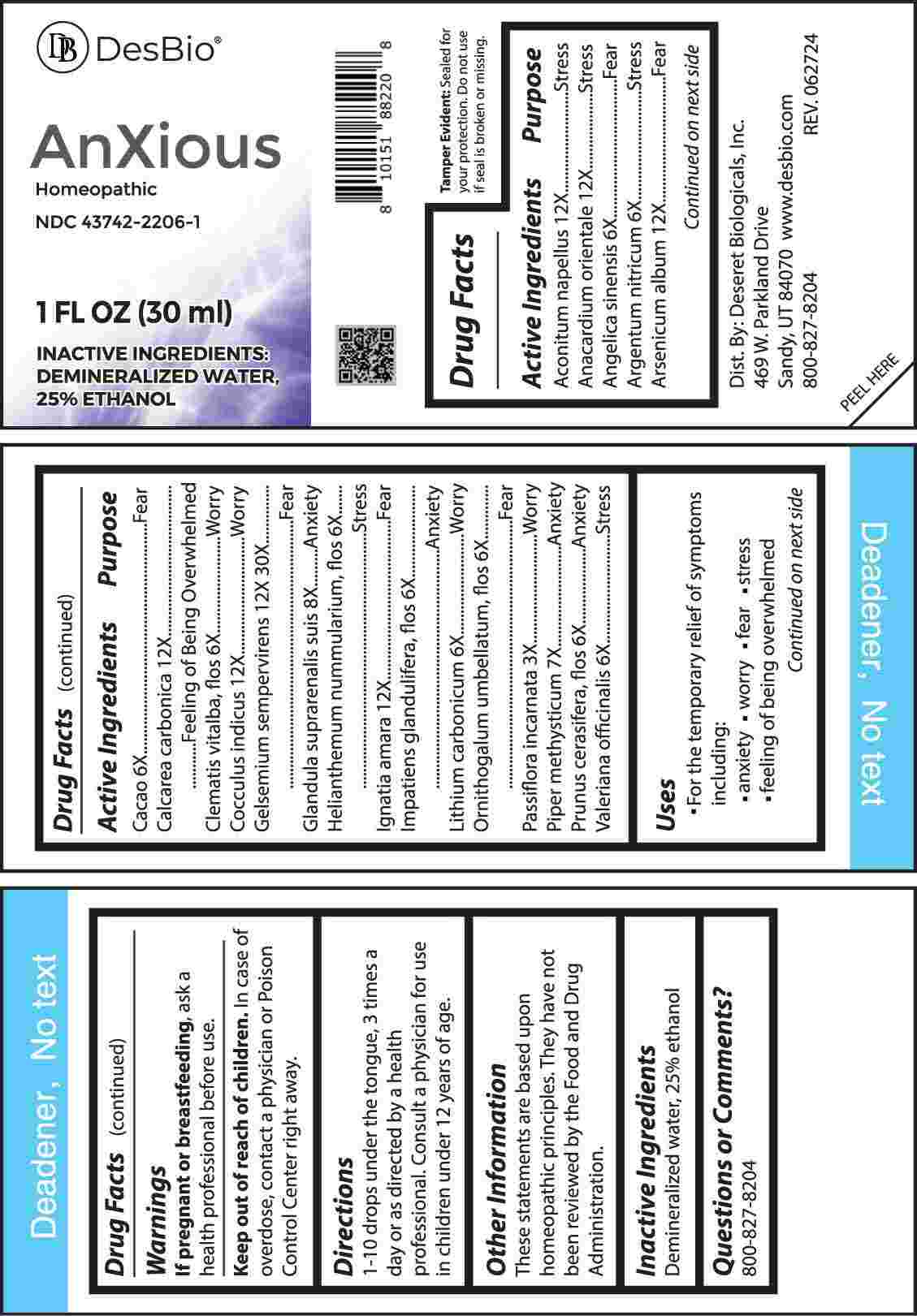 DRUG LABEL: AnXious
NDC: 43742-2206 | Form: LIQUID
Manufacturer: Deseret Biologicals, Inc.
Category: homeopathic | Type: HUMAN OTC DRUG LABEL
Date: 20241108

ACTIVE INGREDIENTS: ACONITUM NAPELLUS WHOLE 12 [hp_X]/1 mL; SEMECARPUS ANACARDIUM JUICE 12 [hp_X]/1 mL; ANGELICA SINENSIS ROOT 6 [hp_X]/1 mL; SILVER NITRATE 6 [hp_X]/1 mL; ARSENIC TRIOXIDE 12 [hp_X]/1 mL; COCOA 6 [hp_X]/1 mL; OYSTER SHELL CALCIUM CARBONATE, CRUDE 12 [hp_X]/1 mL; CLEMATIS VITALBA FLOWER 6 [hp_X]/1 mL; ANAMIRTA COCCULUS SEED 12 [hp_X]/1 mL; GELSEMIUM SEMPERVIRENS ROOT 12 [hp_X]/1 mL; SUS SCROFA ADRENAL GLAND 8 [hp_X]/1 mL; HELIANTHEMUM NUMMULARIUM FLOWER 6 [hp_X]/1 mL; STRYCHNOS IGNATII SEED 12 [hp_X]/1 mL; IMPATIENS GLANDULIFERA FLOWER 6 [hp_X]/1 mL; LITHIUM CARBONATE 6 [hp_X]/1 mL; ORNITHOGALUM UMBELLATUM FLOWERING TOP 6 [hp_X]/1 mL; PASSIFLORA INCARNATA FLOWERING TOP 3 [hp_X]/1 mL; PIPER METHYSTICUM ROOT 7 [hp_X]/1 mL; PRUNUS CERASIFERA FLOWER 6 [hp_X]/1 mL; VALERIAN 6 [hp_X]/1 mL
INACTIVE INGREDIENTS: WATER; ALCOHOL

DRUG FACTS:

ACTIVE INGREDIENTS:

Aconitum Napellus 12X, Anacardium Orientale 12X, Angelica Sinensis 6X, Argentum Nitricum 6X, Arsenicum Album 12X, Cacao 6X, Calcarea Carbonica 12X, Clematis Vitalba, Flos 6X, Cocculus Indicus 12X, Gelsemium Sempervirens 12X, 30X, Glandula Suprarenalis Suis 8X, Helianthemum Nummularium, Flos 6X, Ignatia Amara 12X, Impatiens Glandulifera, Flos 6X, Lithium Carbonicum 6X, Ornithogalum Umbellatum, Flos 6X, Passiflora Incarnata 3X, Piper Methysticum 7X, Prunus Cerasifera, Flos 6X, Valeriana Officinalis 6X

PURPOSE:

Aconitum Napellus - Stress, Anacardium Orientale - Stress, Angelica Sinensis - Fear, Argentum Nitricum - Stress, Arsenicum Album - Fear, Cacao - Fear, Calcarea Carbonica – Feeling of Being Overwhelmed, Clematis Vitalba, Flos - Worry, Cocculus Indicus - Worry, Gelsemium Sempervirens - Fear, Glandula Suprarenalis Suis - Anxiety, Helianthemum Nummularium, Flos - Stress, Ignatia Amara - Fear, Impatiens Glandulifera, Flos - Anxiety, Lithium Carbonicum - Worry, Ornithogalum Umbellatum Flos, - Fear, Passiflora Incarnata - Worry, Piper Methysticum - Anxiety, Prunus Cerasifera, Flos 6X - Anxiety, Valeriana Officinalis - Stress.

USES:

• For the temporary relief of symptoms including:

• anxiety • worry • fear • stress

• feeling of being overwhelmed

These statements are based upon homeopathic principles. They have not been reviewed by the Food and Drug Administration.

WARNINGS:

If pregnant or breast-feeding, ask a health professional before use.

Keep out of reach of children. In case of overdose, contact a physician or Poison Control Center right away.
Tamper Evident: Sealed for your protection. Do not use if seal is broken or missing.

KEEP OUT OF REACH OF CHILDREN:

In case of overdose, contact a physician or Poison Control Center right away.

DIRECTIONS:

1-10 drops under the tongue, 3 times a day or as directed by a health professional. Consult a physician for use in children under 12 years of age.

INACTIVE INGREDIENTS:

Demineralized water, 25% ethanol

QUESTIONS:

Dist. By: Deseret Biologicals, Inc.
469 W. Parkland Drive
Sandy, UT 84070 www.desbio.com

800-827-8204

PACKAGE LABEL DISPLAY:

DesBio

AnXious

Homeopathic

NDC 43742-2206-1

1 FL OZ (30 ml)